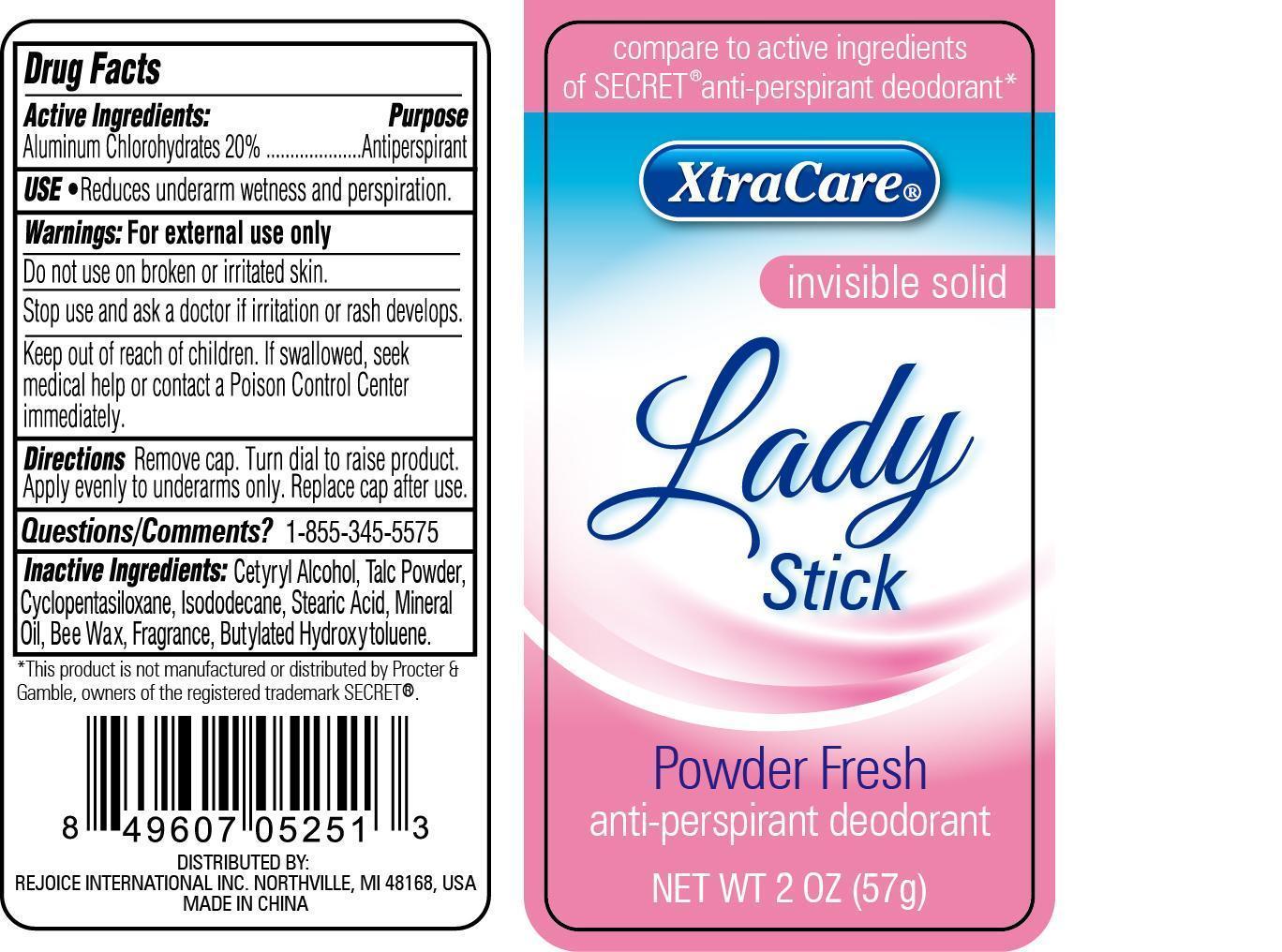 DRUG LABEL: XtraCare Invisible Solid Lady Stick Powder Fresh
NDC: 57337-042 | Form: CREAM
Manufacturer: Rejoice International
Category: otc | Type: HUMAN OTC DRUG LABEL
Date: 20240228

ACTIVE INGREDIENTS: ALUMINUM CHLOROHYDRATE 11 g/57 g
INACTIVE INGREDIENTS: CETYL ALCOHOL; TALC; CYCLOMETHICONE 5; ISODODECANE; STEARIC ACID; MINERAL OIL; YELLOW WAX; BUTYLATED HYDROXYTOLUENE

XtraCare Invisible Solid Lady Stick Powder Fresh

Active Ingredients Purpose

Aluminum Chlorohydrates 20% .............. Antiperspirant

Uses

reduces underarm wetness and perspiration

Keep out of reach of children. If swallowed, seek medical help or contact a Poison Control Center right away.

INDICATIONS AND USAGE

compare to active ingredients of SECRET® anti-perspirant deodorant*

XtraCare® invisible solid Lady Stick

Powder Fresh anti-perspirant deodorant

Net Wt 2 oz (57g)

Warnings: For external use only

Do not use on broken or irritated skin.

Stop use and ask a doctor if irritation or rash develops.

Directions

Remove cap. Turn dial to raise product. Apply evenly to underarms only. Replace cap after use.

INACTIVE INGREDIENT

Inactive Ingredients: cetyryl alcohol, talc powder, cyclopentasiloxane, isododecane, stearic acid, mineral oil, bee wax, fragrance, butylated hydroxytoluene.

OTHER SAFETY INFORMATION

Questions/Comments? 1-855-345-5575

*This product is not manufactured or distributed by Procter & Gamble, owners of the registered trademark SECRET®.

DISTRIBUTED BY:

REJOICE INTERNATIONAL INC. NORTHVILLE, MI 48168, USA

MADE IN CHINA